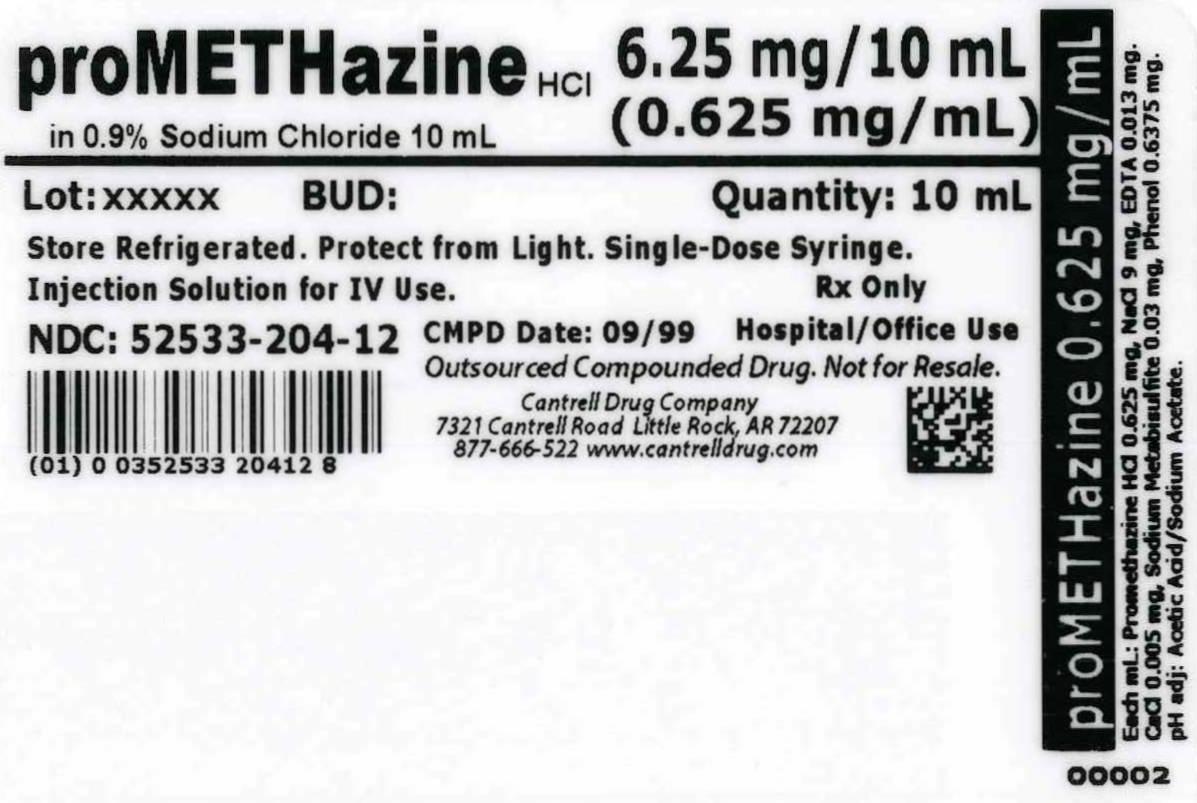 DRUG LABEL: Promethazine HCl
NDC: 52533-204 | Form: INJECTION, SOLUTION
Manufacturer: Cantrell Drug Company
Category: prescription | Type: HUMAN PRESCRIPTION DRUG LABEL
Date: 20140527

ACTIVE INGREDIENTS: PROMETHAZINE HYDROCHLORIDE 0.625 mg/1 mL
INACTIVE INGREDIENTS: SODIUM CHLORIDE 9 mg/1 mL; EDETATE SODIUM 0.013 mg/1 mL; CALCIUM CHLORIDE 0.005 mg/1 mL; SODIUM METABISULFITE 0.03 mg/1 mL; PHENOL 0.6375 mg/1 mL; WATER

Promethazine HCl 0.625 mg/mL in 0.9% Sodium Chloride 10 mL Syringe